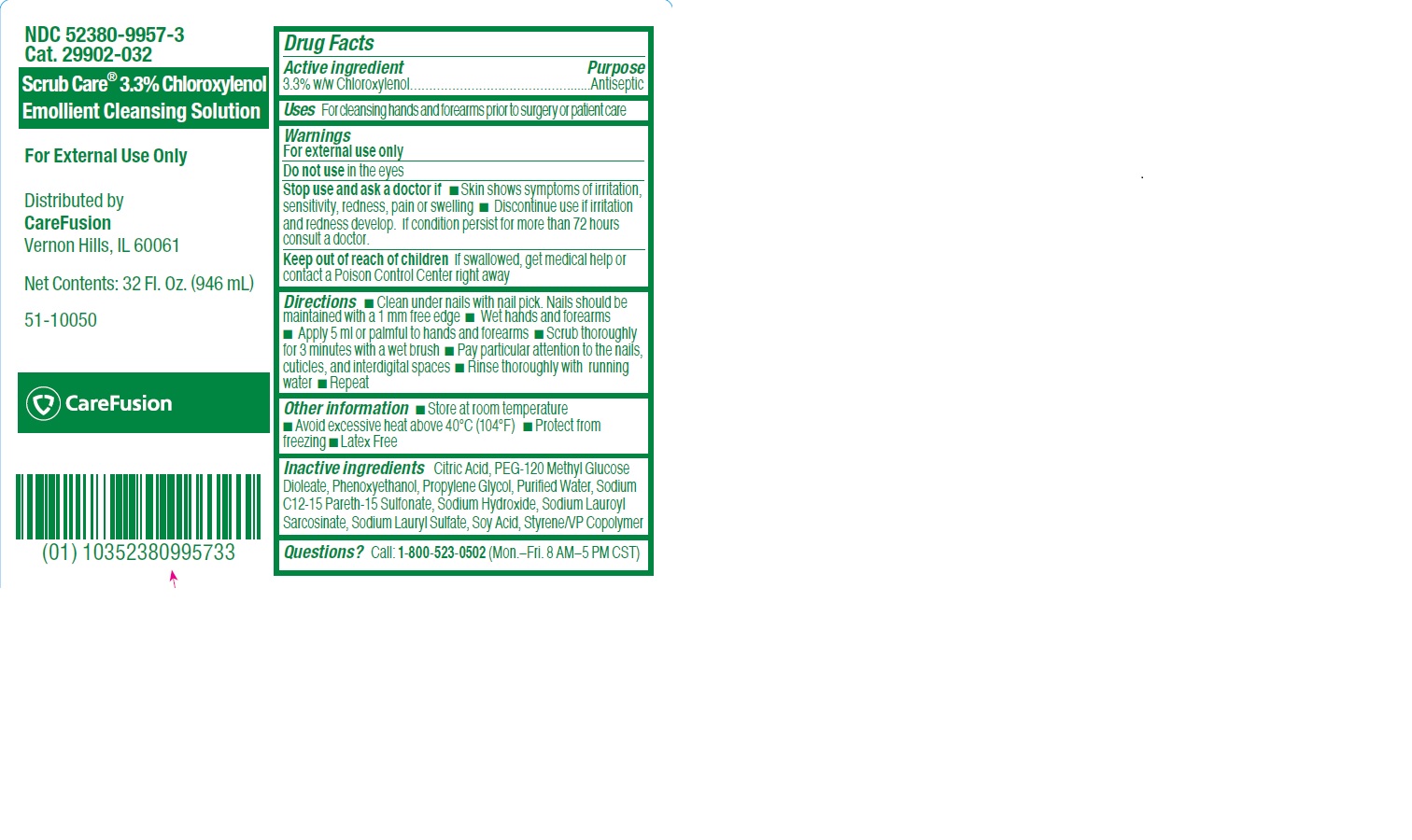 DRUG LABEL: PCMX with Emollient
NDC: 52380-9957 | Form: SOLUTION
Manufacturer: Aplicare Products, LLC.
Category: otc | Type: HUMAN OTC DRUG LABEL
Date: 20180220

ACTIVE INGREDIENTS: CHLOROXYLENOL 3.3 mg/100 mL
INACTIVE INGREDIENTS: SODIUM C12-15 PARETH-15 SULFONATE; SOY ACID; PEG-120 METHYL GLUCOSE DIOLEATE; WATER; SODIUM LAUROYL SARCOSINATE; PROPYLENE GLYCOL; SODIUM LAURYL SULFATE; PHENOXYETHANOL; ANHYDROUS CITRIC ACID; SODIUM HYDROXIDE

PCMX with Emollient

ACTIVE INGREDIENT

3.3% w/w Chloroxylenol

Uses

For cleansing hands and forearms prior to surgery or patient care

PURPOSE

Antiseptic

WARNINGS

For external use only

Do not use in the eyes

Stop use and ask a doctor if

- skin shows symptoms of irritation, sensitivity, redness, pain or swelling
- discontinue use if irritation and redness develop. If condition persists more than 72 hours consult a doctor.

Keep out of reach of children. If swallowed, get medical help or contact a Poison Control Center right away.

Directions

- Clean under nails with nail pick. Nails should be maintained with a 1 mm free edge
- Wet hands and forearms
- Apply 5 ml or palmful to hands and forearms
- Scrub thoroughly for 3 minutes with a wet brush
- Pay particular attention to the nails, cuticles and interdigital spaces
- Rinse thoroughly with running water
- Repeat

Other information

- Store at room temperature
- Avoid excessive heat above 40 deg C (104 deg F)
- Protect from freezing
- Latex Free

INACTIVE INGREDIENT

Citric Acid, PEG-120 Methyl Glucose Dioleate, Phenoxyethanol, Propylene Glycol, Purified Water, Sodium C12-15 Pareth-15 Sulfonate, Sodium Hydroxide, Sodium Lauroyl Sarcosinate, Sodium Laryl Sulfate, Soy Acid, Styrene/VP Copolymer

Questions?

Call: 1-800-523-0502 (Mon. - Fri. 8 AM-5 PM CST)

PACKAGE LABEL

Scrub Care 3.3% Chloroxylenol

Emmollient CLeansing Solution